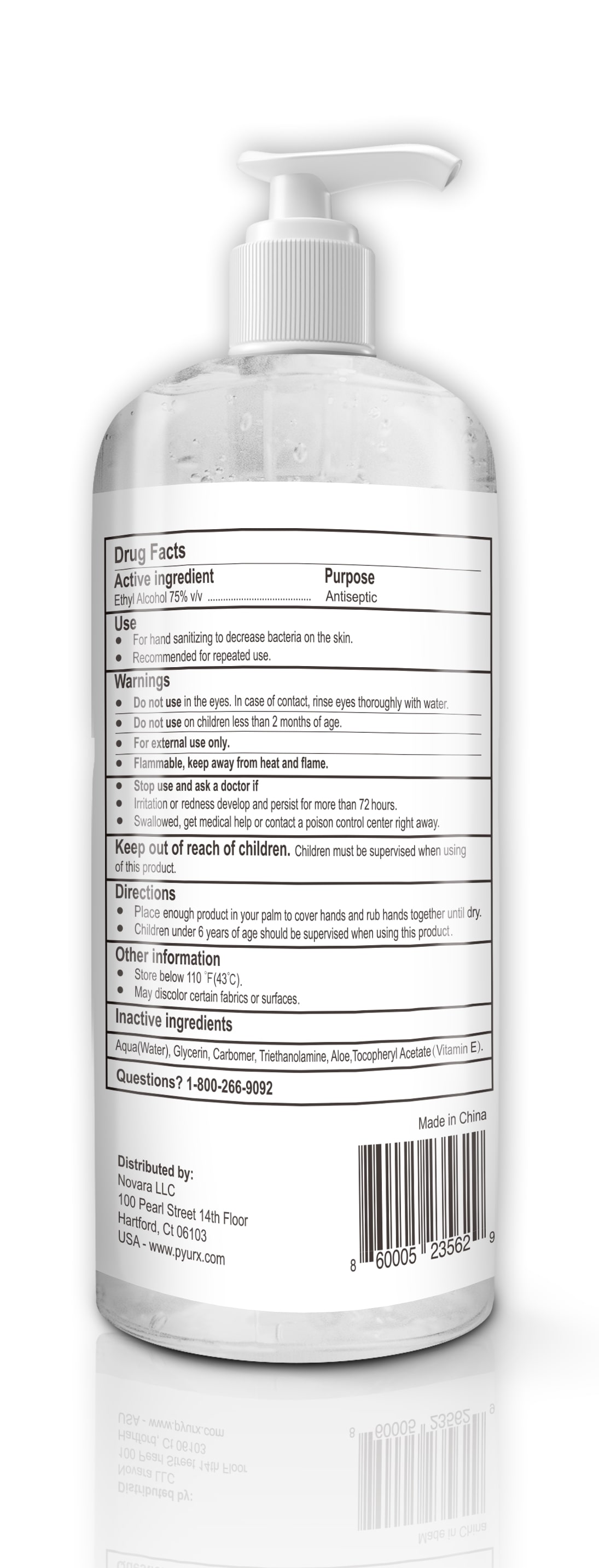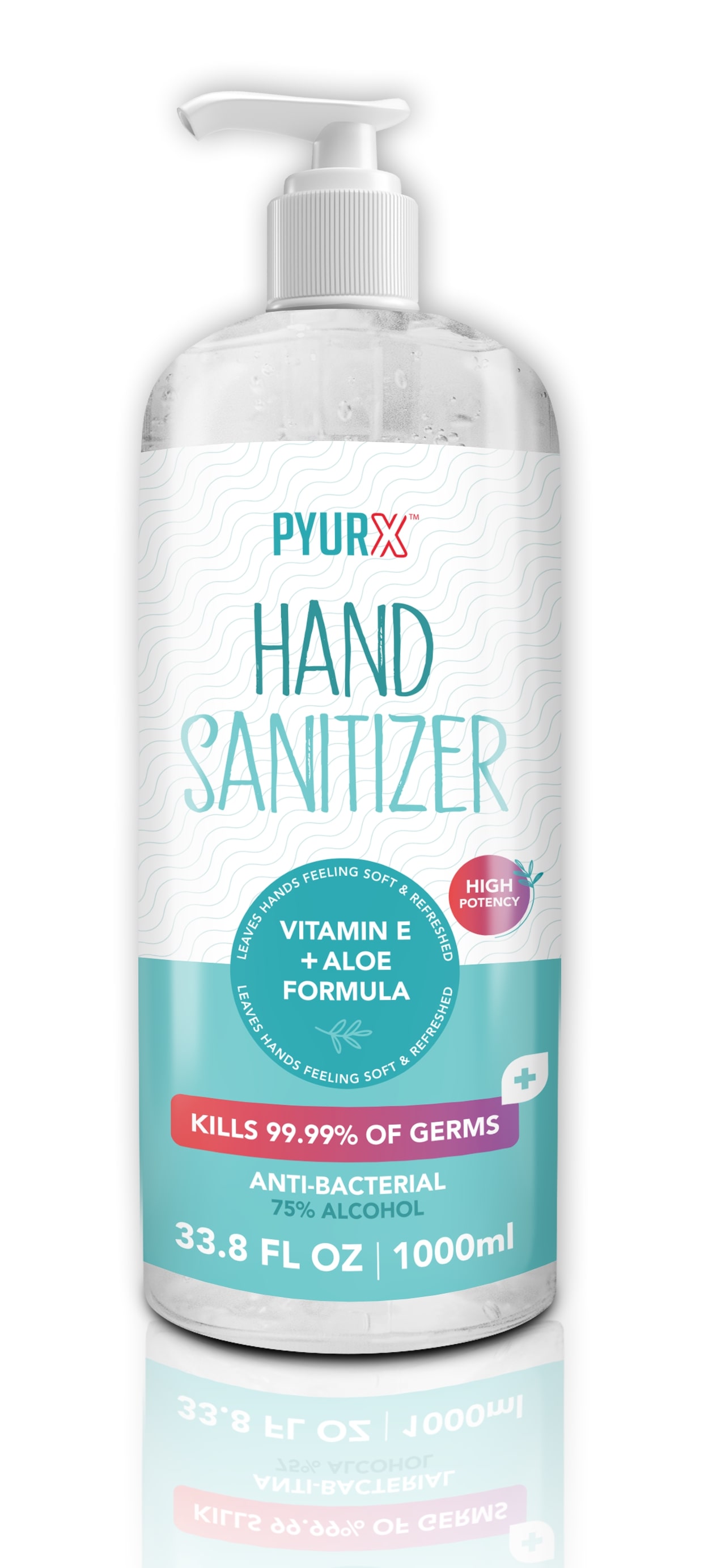 DRUG LABEL: PyurX
NDC: 80527-252 | Form: GEL
Manufacturer: Novara LLC
Category: otc | Type: HUMAN OTC DRUG LABEL
Date: 20200915

ACTIVE INGREDIENTS: ALCOHOL 75 mL/100 mL
INACTIVE INGREDIENTS: WATER 13.8 mL/100 mL; TROLAMINE 4 mL/100 mL; GLYCERIN 3 mL/100 mL; ALOE 0.1 mL/100 mL; ALPHA-TOCOPHEROL ACETATE 0.1 mL/100 mL; CARBOMER HOMOPOLYMER, UNSPECIFIED TYPE 4 mL/100 mL

This is a hand sanitizer manufactured according to the Temporary Policy for Preparation of Certain Alcohol-Based Hand Sanitizer Products During the Public Health Emergency (CoViD-19); Guidance for Industry.

The hand sanitizer is manufactured using only the following United States Pharmacopoeia (USP) grade ingredients in the preparation of the product (percentage in final product formulation) consistent with World Health Organization (WHO) recommendations:

Isopropyl Alcohol (75%, v/v) in an aqueous solution denatured according to Alcohol and Tobacco Tax and Trade Bureau regulations in 27 CFR part 20.
Glycerol (1.45% v/v).
Hydrogen peroxide (0.125% v/v).
Sterile distilled water or boiled cold water.

The firm does not add other active or inactive ingredients. Different or additional ingredients may impact the quality and potency of the product.

SEE INGREDIENTS LIST FOR ACCURATE LIST

Active Ingredient(s)

Ethyl Alcohol 75% v/v. Purpose: Antiseptic

Purpose

Antiseptic, Hand Sanitizer

Use

- For hand washing to decrease bacteria on the skin.
- Recommended for repeated use.

Warnings

- For external use only.
- Flammable, keep away from heart and flame.

- Do not use in the eyes. In case of contact, rinse eyes thoroughly with water.
- Do not use on children less than 2 months of age.

Stop use and ask a doctor if

- Irritaion, and redness develop and persist for more than 72 hours.
- Swallowed, get medical help or contact a poison control center right away.

Keep out of reach of children. Children must be supervised in use of this product.

Directions

- Place enough product in your palm to cover hands and rub hands together until dry.
- Children under 6 years of age should be supervised when using this product.

Other information

- Store below 110F (43C)
- May discolor certain fabrics or surfaces

Inactive ingredients

Aqua(water), Glycerin, Carbomer, Triethanolamine, Aloe, Tocopheryl Acetate (Vitamin E).